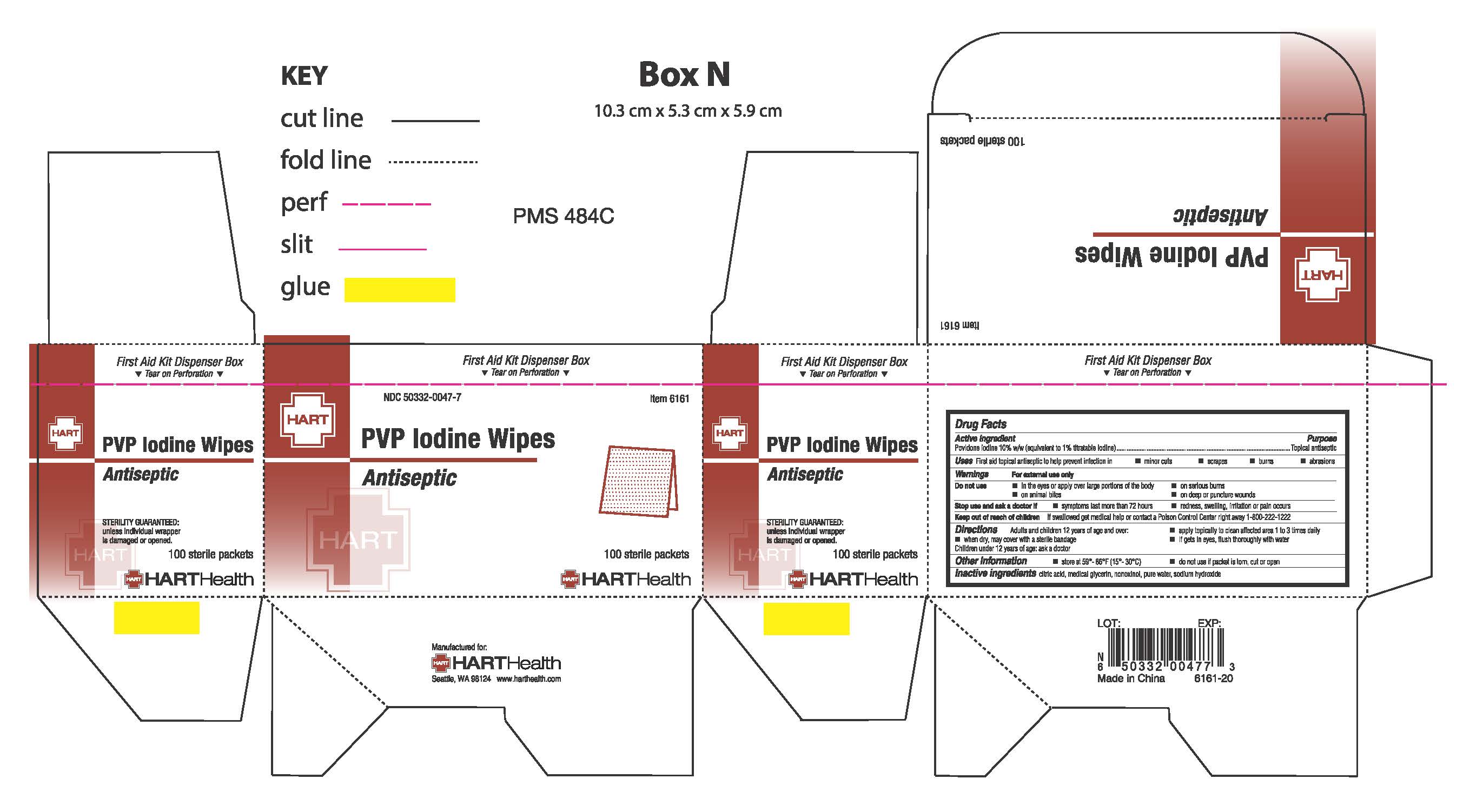 DRUG LABEL: PVP Iodine
NDC: 50332-0047 | Form: SWAB
Manufacturer: HART Health
Category: otc | Type: HUMAN OTC DRUG LABEL
Date: 20251231

ACTIVE INGREDIENTS: POVIDONE-IODINE .10 g/1 g
INACTIVE INGREDIENTS: CITRIC ACID ACETATE; GLYCERIN; NONOXYNOL-9; SODIUM HYDROXIDE; WATER

PVP IODINE WIPES

Active Ingredient

Povidone Iodine 10% (equivalent to 1% titratable iodine)

Purpose

Topical Antiseptic

Uses

First aid topical antiseptic to help prevent infection in:

- minor cuts
- scrapes
- burns
- abrasions

Warnings

For external use only

Do not use

- in the eyes or over large portions of the body
- on serious burns
- on animal bites
- on deep or puncture wounds

Stop use and ask a doctor if

- symptoms last more than 72 hours
- redness, swelling, irritation or pain occurs

Keep out of reach of children

If swallowed get medical help or contact a Poison Control Center right away 1-800-222-1222

Directions

Adults and children 12 years of age and over:

- apply topically to clean affected area 1 to 3 times daily
- when dry, may be covered with a sterile bandage
- if gets in eyes, flush thoroughly with water

Children under 12 years of age:

- ask a doctor

Inactive Ingredients

Citric Acid, Glyercin, Nonoxynol, Sodium Hydroxide, Water